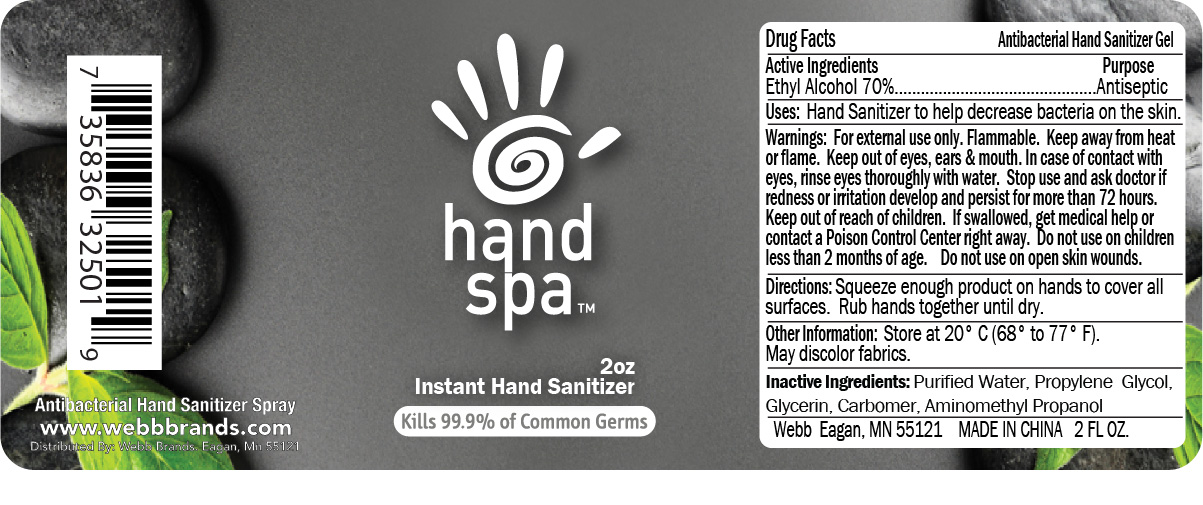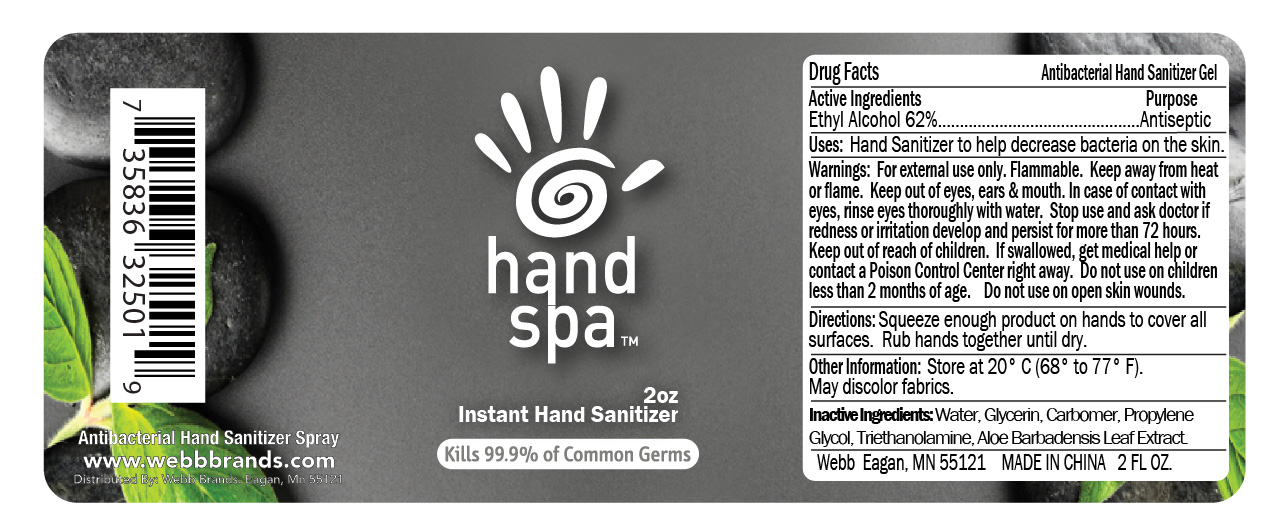 DRUG LABEL: Antibacterial Hand Sanitizer
NDC: 70445-415 | Form: GEL
Manufacturer: Webb Business Promotions, Inc
Category: otc | Type: HUMAN OTC DRUG LABEL
Date: 20220104

ACTIVE INGREDIENTS: ALCOHOL 70 mL/100 mL
INACTIVE INGREDIENTS: AMINOMETHYL PROPANEDIOL; PROPYLENE GLYCOL; CARBOMER 940; GLYCERIN; WATER

Antibacterial Hand Sanitizer Gel

WARNINGS

For external use only. Flammable. Keep away from het or flame. Keep out of eyes, ears, and mouth. In case of contact with eyes, rinse eyes thoroughly with water. If swallowed, get medical help or contact a poison Control Center right away.

Do not use on children less than 2 months of age. Do not use on open skin wounds.

INACTIVE INGREDIENT

Inactive ingredients: Water, Glycerin, Carbomer, Propylene Glycol, Triethanolamine, Aloe Barbadense Leaf Extract

PURPOSE

Antiseptic

ACTIVE INGREDIENT

Ethyl Alcohol 62%

Keep out of reach of children.

Stop use and ask doctor if redness or irritation develop and persist for more than 72 hours.

OTHER SAFETY INFORMATION

Store at 20 C (68 to 77 F). May discolore fabrics.

Direction

Squeeze enough product on hands to cover all surfaces. Rub hands together until dry.

Uses

Hand Sanitizer to help decrease bacteria on the skin

PACKAGE LABEL

60 ml (2 oz). NDC 70445-415-20